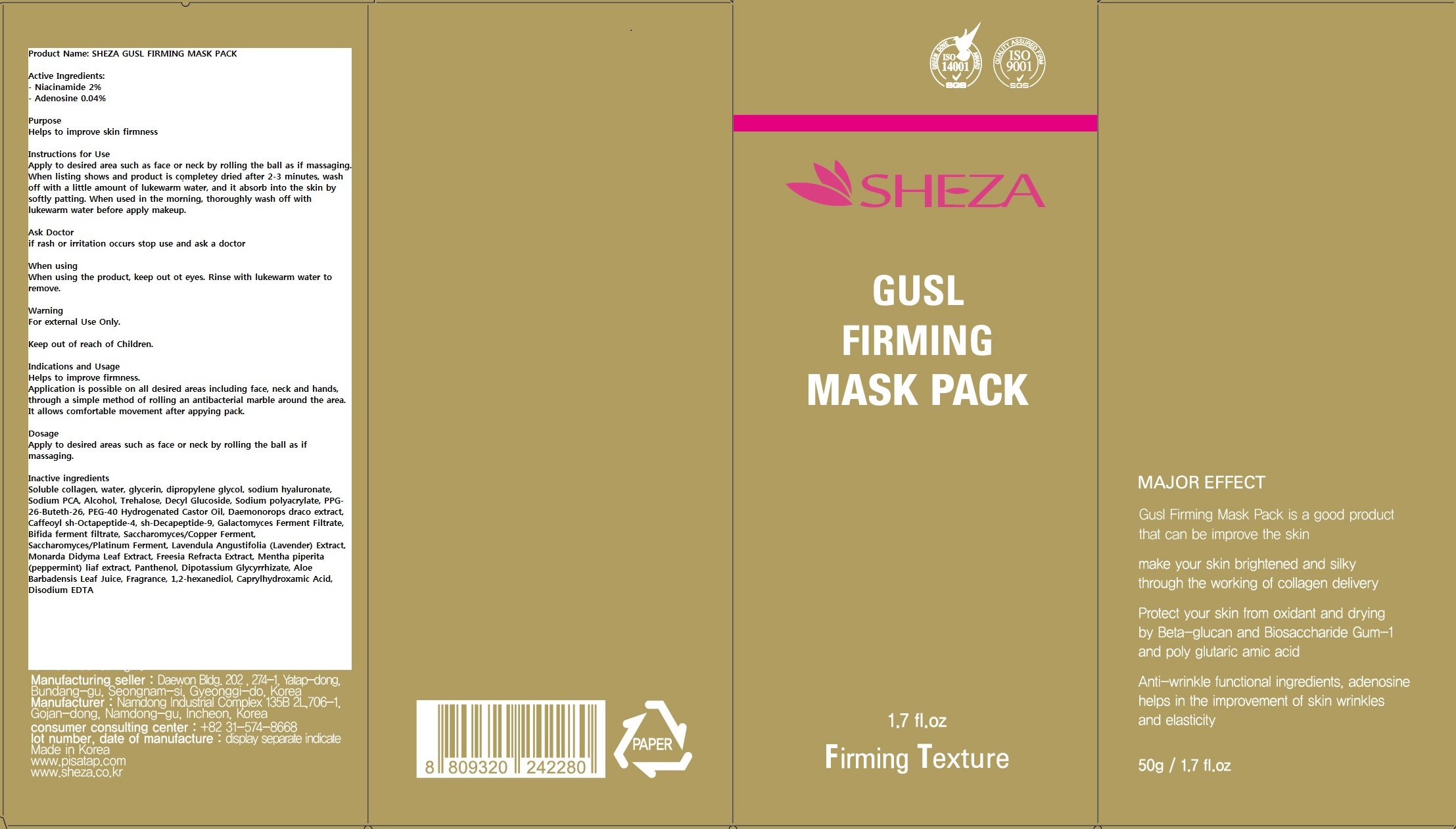 DRUG LABEL: SHEZA GUSL FIRMING MASK PACK
NDC: 59532-001 | Form: CREAM
Manufacturer: PISATAP
Category: otc | Type: HUMAN OTC DRUG LABEL
Date: 20130809

ACTIVE INGREDIENTS: Niacinamide 1 g/50 g; Adenosine 0.02 g/50 g
INACTIVE INGREDIENTS: PORK COLLAGEN; Water; Glycerin; Dipropylene Glycol; HYALURONATE SODIUM; SODIUM PYRROLIDONE CARBOXYLATE; Alcohol; Trehalose; Decyl Glucoside; SODIUM POLYACRYLATE (8000 MW); PPG-26-Buteth-26; POLYOXYL 40 HYDROGENATED CASTOR OIL; DAEMONOROPS DRACO WHOLE; SACCHAROMYCES CEREVISIAE; LAVANDULA ANGUSTIFOLIA FLOWERING TOP; MONARDA DIDYMA LEAF; FREESIA ALBA FLOWER; MENTHA PIPERITA LEAF; CHAMOMILE; ROSEMARY; Panthenol; GLYCYRRHIZINATE DIPOTASSIUM; ALOE VERA LEAF; 1,2-Hexanediol; CAPRYLHYDROXAMIC ACID; EDETATE DISODIUM

Drug Facts

ACTIVE INGREDIENT

Niacinamide 2%

Adenosine 0.04%

PURPOSE

Helps to improve skin firmness

INSTRUCTIONS FOR USE

Apply to desired area such as face or neck by rolling the ball as if massaging. When lifting shows and product is completely dried after 2-3 minutes, wash off with a little amount of lukewarm water, and it absorb into the skin by softly patting.

When used in the morning, thoroughly wash off with lukewarm water before apply makeup.

ASK DOCTOR

If rash or irritation occurs, stop use and ask a doctor.

WHEN USING

When using the product, keep out of eyes. Rinse with lukewarm water to remove.

INACTIVE INGREDIENT

Soluble collagen, water, glycerin, dipropylene Glycol, Sodium Hyaluronate, Sodium PCA, Alcohol, Trehalose, Decyl Glucoside, Sodium polyacrylate, PPG-26-Buteth-26, PEG-40 Hydrogenated Castor Oil, Daemonorops draco extract, Caffeoyl sh-Octapeptide-4, sh-Decapeptide-9, Galactomyces Ferment Filtrate, Bifida ferment filtrate, Saccharomyces/Copper Ferment, Saccharomyces/Platinum Ferment, Lavendula Angustifolia (Lavender) Extract, Monarda Didyma Leaf Extract, Freesia Refracta Extract,Mentha piperita (peppermint) leaf extract, Chamomilla recutita (Matricaria) flower extract, Rosmarinus Officinalis (Rosemary) leaf extract, Panthenol, Dipotassium Glycyrrhizate, Aloe Barbadensis Leaf Juice, Fragrance, 1-2-hexanediol, Caprylhydroxamic Acid, Disodium EDTA

WARNINGS

For External Use Only.

Keep out of reach of children.

INDICATIONS AND USAGE

Helps to improve firmness.

Application is possible on all desired areas including face, neck, and hands, through a simple method of rolling an antibacterial marble around the area.

It allows comfortable movement after applying pack.

DOSAGE AND ADMINISTRATION

Apply to desired areas such as face or neck by rolling the ball as if massaging.